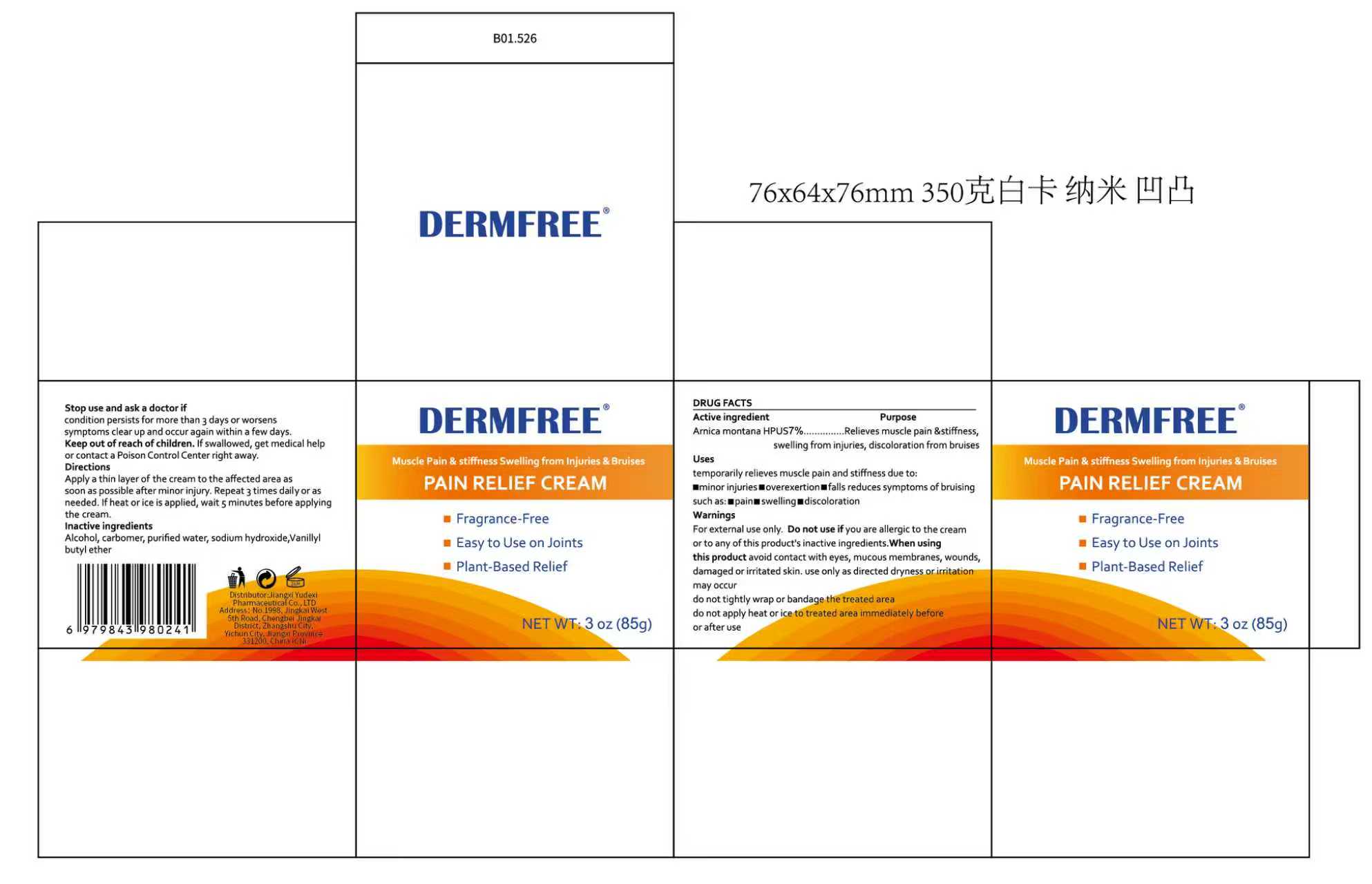 DRUG LABEL: DERMFREE PAIN RELIEF
NDC: 85248-145 | Form: CREAM
Manufacturer: Jiangxi Yudexi Pharmaceutical Co., LTD
Category: otc | Type: HUMAN OTC DRUG LABEL
Date: 20260226

ACTIVE INGREDIENTS: ARNICA MONTANA 7 g/100 g
INACTIVE INGREDIENTS: ALCOHOL; SODIUM HYDROXIDE; VANILLYL BUTYL ETHER; WATER; CARBOMER

85248-145

Active Ingredient

Arnica montana HPUS 7%

Purpose

Relieves muscle pain & stiffness，swelling from injuries, discoloration from bruises

Use

temporarily relieves muscle pain and stiffness due to: ■Minor injuries ■Overexertion
■falls reduces symptoms of bruising such as: ■Pain■Swelling ■Discoloration

Warnings

For external use only

Do not use if you are allergic to the cream or to any of this product's inactive ingredients.

When Using

When using this product avoid contact with eyes, mucous membranes, wounds，damaged or irritated skin.Use only as directed .Dryness or irritation may occur.
Do not tightly wrap or bandage the treated area. Do not apply heat or ice to treated area immediately before or after use

Stop Use

if condition persists for more than 3 days or worsens, symptoms clear up and occur again within a few days.

Ask Doctor

if condition persists for more than 3 days or worsens, symptoms clear up and occur again within a few days.

Keep Oot Of Reach Of Children

If swallowed, get medical help or contact a Poison Control Center right away.

Directions

Apply a thin layer of the cream to the affected area as soon as possible after minor injury. Repeat 3 times daily or as needed.If heat or ice is applied, wait 5 minutes before applying the cream.

Inactive ingredients

purified water, alcohol, carbomer,sodium hydroxide, Vanilly butyl ether